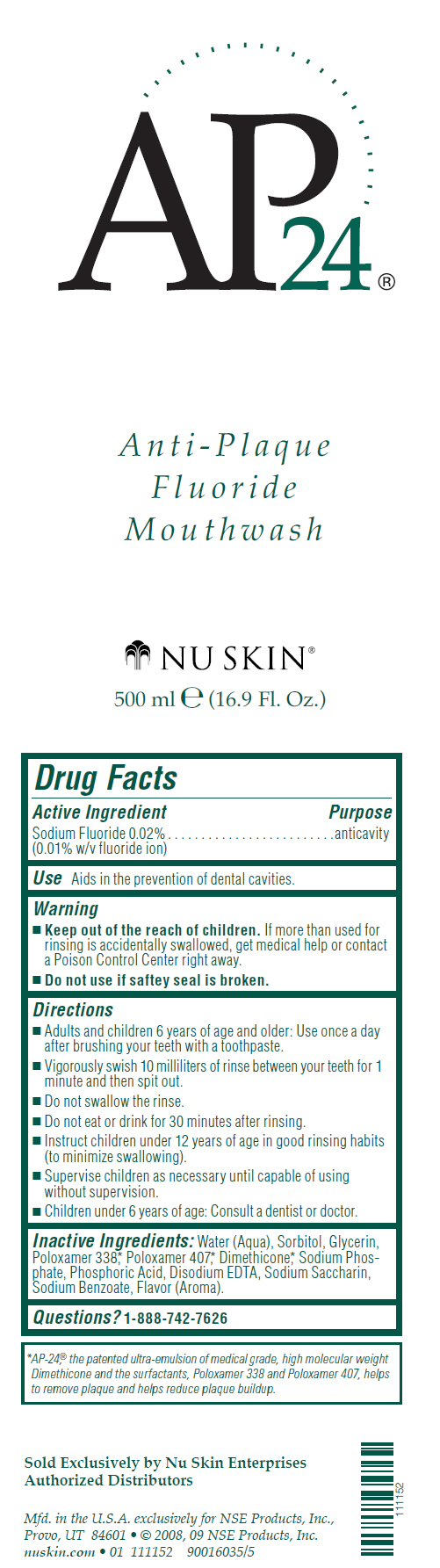 DRUG LABEL: AP-24
NDC: 62839-1152 | Form: MOUTHWASH
Manufacturer: NSE Products, Inc
Category: otc | Type: HUMAN OTC DRUG LABEL
Date: 20250107

ACTIVE INGREDIENTS: Sodium Fluoride 0.2 mg/1 mL
INACTIVE INGREDIENTS: Water; Sorbitol; Glycerin; Poloxamer 338; Poloxamer 407; Dimethicone; Sodium Phosphate; Phosphoric Acid; Edetate Disodium Anhydrous; Saccharin Sodium; Sodium Benzoate

AP-24® Mouthwash

Drug Facts

Active Ingredient

Sodium Fluoride 0.02% (0.01% w/v fluoride ion)

Purpose

anticavity

Use

Aids in the prevention of dental cavities.

Warning

KEEP OUT OF REACH OF CHILDREN

- Keep out of the reach of children. If more than used for rinsing is accidentally swallowed, get medical help or contact a Poison Control Center right away.

- Do not use if saftey seal is broken.

Directions

- Adults and children 6 years of age and older: Use once a day after brushing your teeth with a toothpaste.
- Vigorously swish 10 milliliters of rinse between your teeth for 1 minute and then spit out.
- Do not swallow the rinse.
- Do not eat or drink for 30 minutes after rinsing.
- Instruct children under 12 years of age in good rinsing habits (to minimize swallowing).
- Supervise children as necessary until capable of using without supervision.
- Children under 6 years of age: Consult a dentist or doctor.

Inactive Ingredients

Water (Aqua), Sorbitol, Glycerin, Poloxamer 338, [AP-24,® the patented ultra-emulsion of medical grade, high molecular weight Dimethicone and the surfactants, Poloxamer 338 and Poloxamer 407, helps to remove plaque and helps reduce plaque buildup.] Poloxamer 407, Dimethicone, Sodium Phosphate, Phosphoric Acid, Disodium EDTA, Sodium Saccharin, Sodium Benzoate, Flavor (Aroma).

Questions?

1-888-742-7626

PRINCIPAL DISPLAY PANEL - 500 ml Bottle Label

AP24®

Anti-Plaque
Fluoride
Mouthwash

NU SKIN®

500 ml e (16.9 Fl. Oz.)